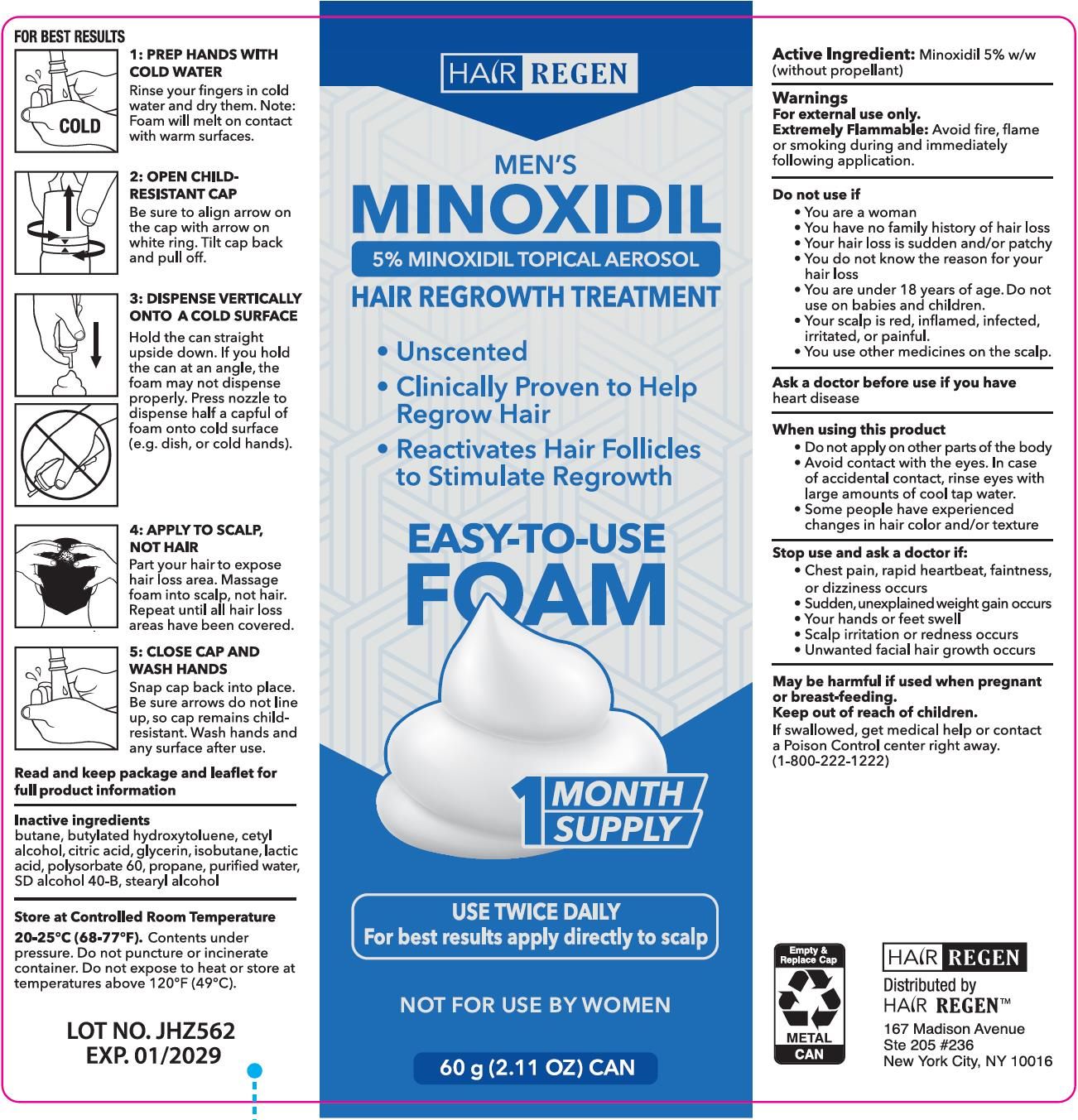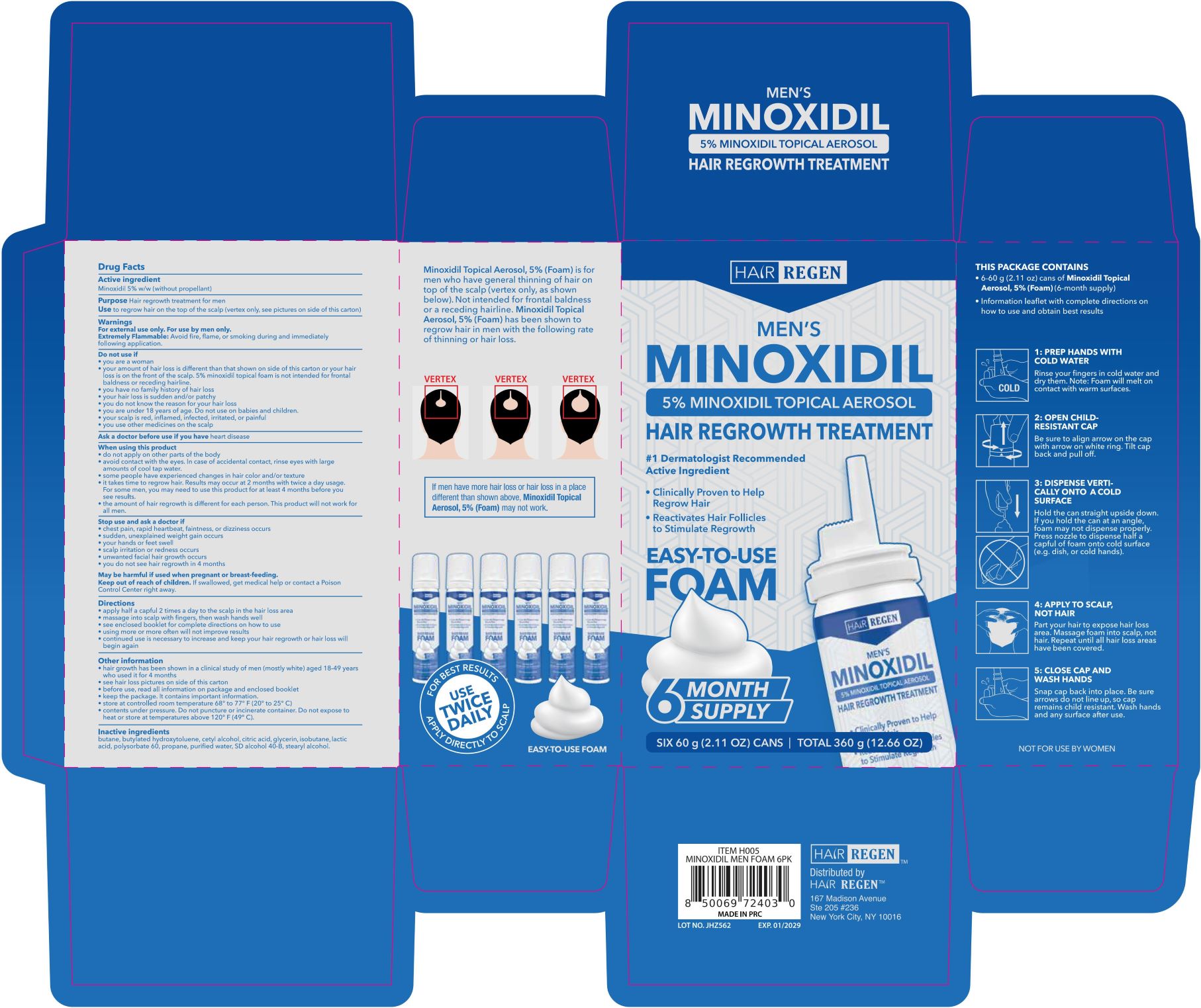 DRUG LABEL: Hair Regen - Hair Regrowth Treatment
NDC: 84232-014 | Form: AEROSOL, FOAM
Manufacturer: Yiwu Yizhou Trading Co., Ltd
Category: otc | Type: HUMAN OTC DRUG LABEL
Date: 20250415

ACTIVE INGREDIENTS: MINOXIDIL 5 g/100 g
INACTIVE INGREDIENTS: GLYCERIN; BUTANE; WATER; ALCOHOL; LACTIC ACID; POLYSORBATE 60; CETYL ALCOHOL; CITRIC ACID; PROPANE; ISOBUTANE; STEARYL ALCOHOL; BUTYLATED HYDROXYTOLUENE

Minoxidil 5% for Hair Regen Mens foam Minoxidil 6 pk

Active Ingredient

Minoxidil 5% w/w (without propellant)

Purpose

Hair regrowth treatment for men

Use

to regrow hair on top of the scalp (vertex only, see pictures on side of this carton)

Warnings

For external use only. For use by men only.

Extremely Flammable: Avoid fire, flame, or smoking during and immediately following application.

Do not use if

- you are a woman.
- your amount of hair loss is different than that shown on the side of this carton or your hair loss is on the front of the scalp. 5% minoxidil topical foam is not intended for frontal baldness or receding hairline.
- you have no family history of hair loss.
- your hair loss is sudden and/or patchy.
- you do not know the reason for your hair loss.
- you are under 18 years of age. Do not use on babies and children.
- your scalp is red, inflamed, infected, irritated, or painful.
- you use other medicines on the scalp.

Ask a doctor before use

if you have heart disease

When using this product

- do not apply on other parts of your body.
- avoid contact with the eyes. In case of accidental contact, rinse eyes with large amounts of cool tap water.
- some people have experienced changes in hair color and/or texture.
- it takes time to regrow hair. Results may occur at 2 months with twice a day usage.
- for some men, you may need to use this product for at least 4 months before you see results.
- the amount of hair regrowth is different for each person. This product will not work for all men.

Stop use and ask a doctor if

- chest pain, rapid heartbeat, faintness, or dizziness occurs.
- sudden, unexplained weight gain occurs.
- your hands or feet swell.
- scalp irritation or redness occurs.
- unwanted facial hair growth occurs.
- you do not see hair growth in 4 months.

Keep out of reach of children.

If swallowed, get medical helf or contact a Poison Control Center right away.

Directions

- apply half a capful 2 times a day to the scalp in the hair loss area.
- massage into scalp with fingers, then wash hands well.
- see enclosed booklet for complete directions on how to use.
- using more or more often will not improve results.
- continued use is necessary to increase and keep your hair regrowth or hair loss will begin again.

Other information

- hair regrowth has been shown in a clinical study of men (mostly white) aged 18-49 years who used it for 4 months.
- see hair loss pictures on side of this carton.
- before use, read all information on package and enclosed booklet.
- keep the package. It contains important information.

STORAGE AND HANDLING

Store at controlled room temperature 68 to 77℉ (20 to 25℃).

Contents under pressure. Do not puncture or incinerate container. Do not expose to heat or store at temperaures above 120℉ (49℃).

Inactive ingredients

butane, butylated hydroxytoluene, cetyl alcohol, citric acid, glycerin, isobutane, lactic acid, polysorbate 60, propane, purified water, SD alcohol 40-B, stearyl alcohol.

PACKAGE LABEL

M15:

M-02: